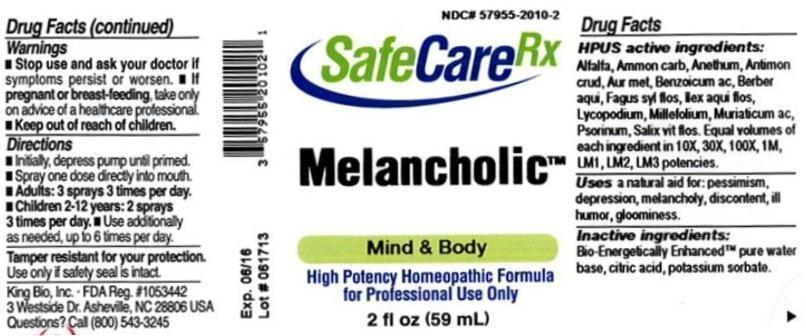 DRUG LABEL: Melancholic
NDC: 57955-2010 | Form: LIQUID
Manufacturer: King Bio Inc.
Category: homeopathic | Type: HUMAN OTC DRUG LABEL
Date: 20130820

ACTIVE INGREDIENTS: ALFALFA 10 [hp_X]/59 mL; AMMONIUM CARBONATE 10 [hp_X]/59 mL; DILL 10 [hp_X]/59 mL; ANTIMONY TRISULFIDE 10 [hp_X]/59 mL; GOLD 10 [hp_X]/59 mL; BENZOIC ACID 10 [hp_X]/59 mL; MAHONIA AQUIFOLIUM ROOT BARK 10 [hp_X]/59 mL; FAGUS SYLVATICA FLOWERING TOP 10 [hp_X]/59 mL; ILEX AQUIFOLIUM FLOWERING TOP 10 [hp_X]/59 mL; LYCOPODIUM CLAVATUM SPORE 10 [hp_X]/59 mL; ACHILLEA MILLEFOLIUM 10 [hp_X]/59 mL; HYDROCHLORIC ACID 10 [hp_X]/59 mL; SCABIES LESION LYSATE (HUMAN) 10 [hp_X]/59 mL; SALIX ALBA FLOWERING TOP 10 [hp_X]/59 mL
INACTIVE INGREDIENTS: WATER; CITRIC ACID MONOHYDRATE; POTASSIUM SORBATE

Melancholic

Drug Facts

____________________________________________________________________________________________________________

HPUS active ingredients: Alfalfa, Ammonium carbonicum, Anethum graveolens, Antimonium crudum, Aurum metallicum, Benzoicum acidum, Berberis aquifolium, Fogus sylvatica, flos, Ilex aquifolium, flos, Lycopodium clavatum, Millefolium, Muriaticum acidum, Psorinum, Salix vitellina, flos. Equal volumes of each ingredient in 10X, 30X, 100X, 1M, LM1, LM2, LM3 potencies.

INDICATIONS AND USAGE

Uses a natural aid for:

- pessimism
- depression
- melancholy
- discontent
- ill humor
- gloominess

INACTIVE INGREDIENT

Inactive ingredients: Bio-Energetically Enhanced pure water base, citric acid, potassium sorbate.

Warnings

- Stop use and ask your doctor if symptoms persist or worsen.
- If pregnant or breast-feeding, take only on advice of a healthcare professional.

- Keep out of reach of children.

Directions:

- Initially, depress pump until primed.
- Spray one dose directly into mouth.
- Adults: 3 sprays 3 times per day.
- Children 2-12 years: 2 sprays 3 times per day.
- Use additionally as needed, up to 6 times per day.

OTHER SAFETY INFORMATION

Tamper resistant for your protection. Use only if safety seal is intact.

PURPOSE

Uses a natural aid for: pessimism, depression, melancholy, discontent, ill humor, gloominess.